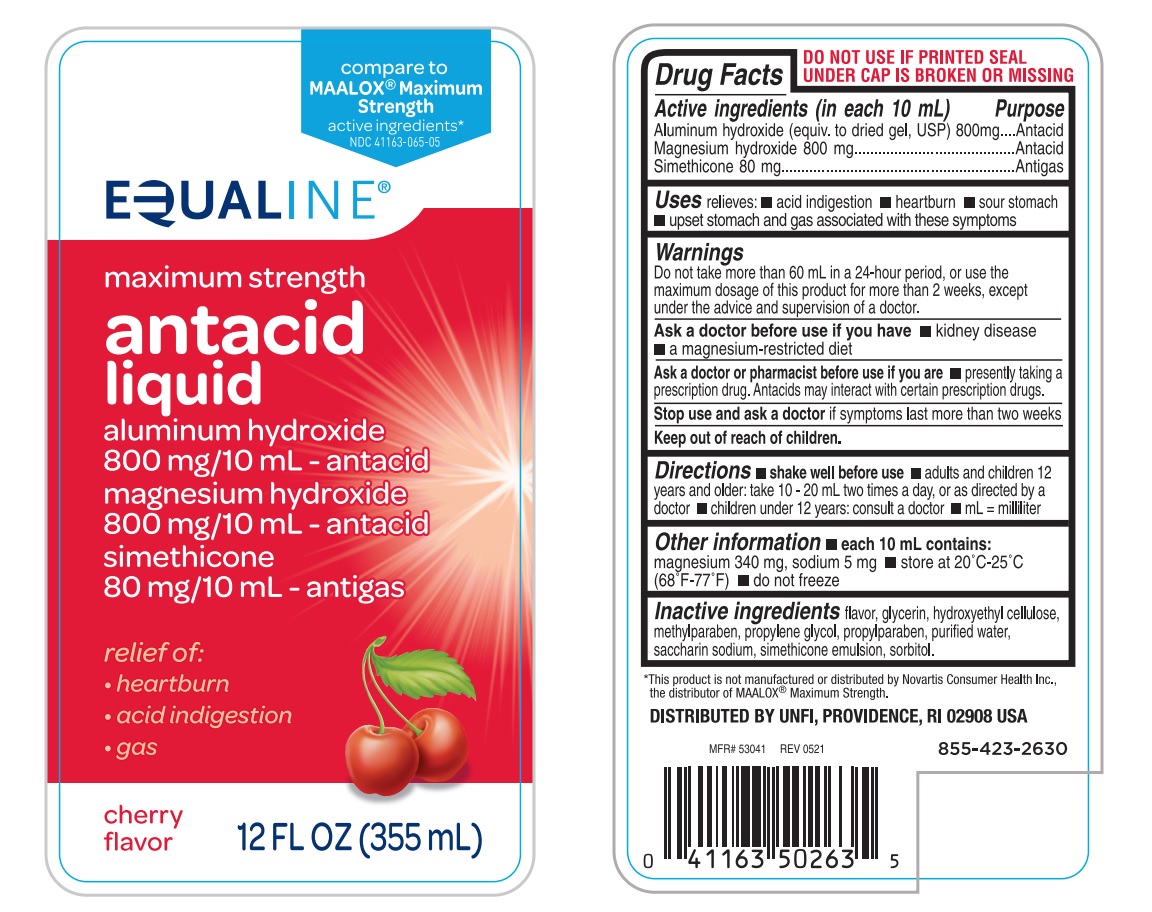 DRUG LABEL: maximum strength antacid cherry
NDC: 41163-065 | Form: LIQUID
Manufacturer: UNITED NATURAL FOODS, INC. DBA UNFI
Category: otc | Type: Human OTC Drug Label
Date: 20241220

ACTIVE INGREDIENTS: aluminum hydroxide 800 mg/10 mL; magnesium hydroxide 800 mg/10 mL; DIMETHICONE 80 mg/10 mL
INACTIVE INGREDIENTS: GLYCERIN; HYDROXYETHYL CELLULOSE, UNSPECIFIED; METHYLPARABEN; PROPYLENE GLYCOL; PROPYLPARABEN; WATER; SACCHARIN SODIUM; SORBITOL

EQUALINE Maximum strength Antacid Cherry

ACTIVE INGREDIENT (in each 10 mL)

Aluminum hydroxide (equiv. to dried gel, USP) 800 mg
Magnesium hydroxide 800 mg
Simethicone 80 mg

PURPOSE

Antacid
Antacid
Antigas

USE(S)

relieves:

- acid indigestion
- heartburn
- sour stomach
- upset stomach and gas associated with these symptoms

WARNINGS

Do not take more than 60 mL in a 24-hour period, or use the maximum dosage of this product for more than 2 weeks, except under the advice and supervision of a doctor.

ASK A DOCTOR BEFORE USE IF YOU HAVE

- kidney disease
- a magnesium-restricted diet

ASK A DOCTOR OR PHARMACIST BEFORE USE IF YOU ARE

- presently taking a prescription drug. Antacids may interact with certain prescription drugs.

STOP USE AND ASK A DOCTOR

if symptoms last more than two weeks

KEEP OUT OF REACH OF CHILDREN

.

DIRECTIONS

- shake well before use
- adults and children 12 years and older: take 10 - 20 mL two times a day, or as directed by a doctor
- children under 12 years: consult a doctor
- mL = milliliter

OTHER INFORMATION

- each 10 mL contains: magnesium 340 mg, sodium 5 mg
- store at 20ºC-25ºC (68ºF-77ºF)
- do not freeze

INACTIVE INGREDIENTS

flavor, glycerin, hydroxyethyl cellulose, methylparaben, propylene glycol, propylparaben, purified water, saccharin sodium, simethicone emulsion, sorbitol

PRINCIPAL DISPLAY PANEL

compare to

MAALOX® Maximum Strength

active ingredients*

NDC 41163-065-05

EQUALINE®

maximum strength

antacid

liquid

aluminum hydroxide

800 mg/10 mL - antacid

Magnesium hydroxide

800 mg/10 mL - antacid

simethicone

80 mg/10 mL - antigas

relief of:

- heartburn
- acid indigestion
- gas

Cherry Flavor

12 FL OZ (355 mL)